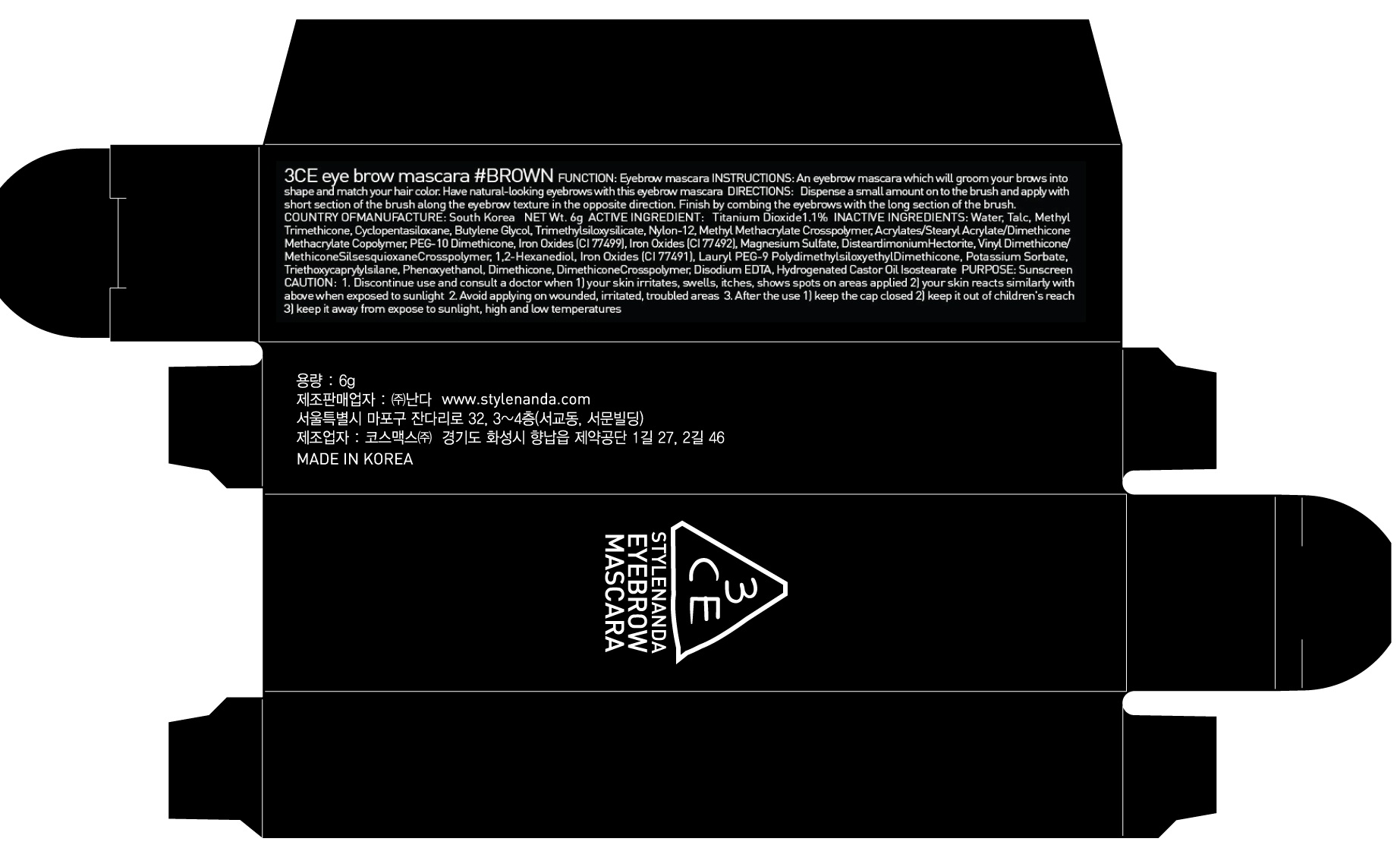 DRUG LABEL: 3CE EYEBROW MASCARA BROWN
NDC: 60764-095 | Form: LIQUID
Manufacturer: Nanda Co., Ltd
Category: otc | Type: HUMAN OTC DRUG LABEL
Date: 20161012

ACTIVE INGREDIENTS: Titanium Dioxide 0.06 g/6 g
INACTIVE INGREDIENTS: Water; Talc

ACTIVE INGREDIENT

Active Ingredient: Titanium Dioxide 1.1%

INACTIVE INGREDIENT

Inactive Ingredients: Water, Talc, Methyl Trimethicone, Cyclopentasiloxane, Butylene Glycol, Trimethylsiloxysilicate, Nylon-12, Methyl Methacrylate Crosspolymer, Acrylates/Stearyl Acrylate/Dimethicone Methacrylate Copolymer, PEG-10 Dimethicone, Iron Oxides (CI 77499), Iron Oxides (CI 77492), Magnesium Sulfate, DisteardimoniumHectorite, Vinyl Dimethicone/MethiconeSilsesquioxaneCrosspolymer, 1,2-Hexanediol, Iron Oxides (CI 77491), Lauryl PEG-9 PolydimethylsiloxyethylDimethicone, Potassium Sorbate, Triethoxycaprylylsilane, Phenoxyethanol, Dimethicone, DimethiconeCrosspolymer, Disodium EDTA, Hydrogenated Castor Oil Isostearate

PURPOSE

Purpose: Sunscreen

CAUTION

CAUTION: 1. Discontinue use and consult a doctor when - your skin irritates, swells, itches, shows spots on areas applied - your skin reacts similarly with above when exposed to sunlight 2. Avoid applying on wounded, irritated, troubled areas 3. After the use - keep the cap closed - keep it out of children's reach - keep it away from expose to sunlight, high and low temperatures

DESCRIPTION

INSTRUCTIONS: An eyebrow mascara which will groom your brows into shape and match your hair color. Have natural-looking eyebrows with this eyebrow mascara

Directions: Dispense a small amount on to the brush and apply with short section of the brush along the eyebrow texture in the opposite direction. Finish by combing the eyebrows with the long section of the brush.